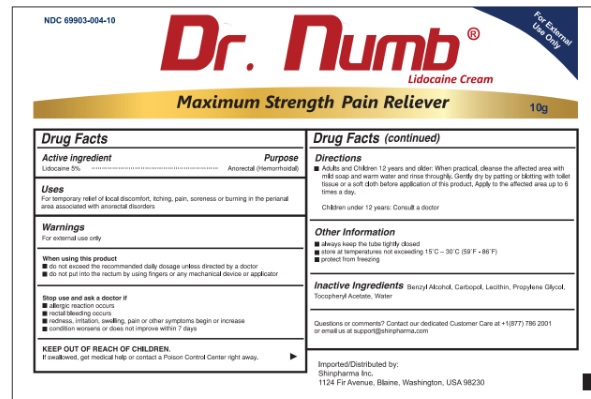 DRUG LABEL: Dr. Numb
NDC: 69903-004 | Form: CREAM
Manufacturer: Shinpharma Inc
Category: otc | Type: HUMAN OTC DRUG LABEL
Date: 20240403

ACTIVE INGREDIENTS: LIDOCAINE 0.5 g/10 g
INACTIVE INGREDIENTS: BENZYL ALCOHOL; CARBOMER HOMOPOLYMER, UNSPECIFIED TYPE; LECITHIN, SOYBEAN; PROPYLENE GLYCOL; .ALPHA.-TOCOPHEROL ACETATE; WATER

Drug Facts

Active ingredient

Lidocaine 5% w/w

Purpose

Anorectal (Hemorrhoidal)

Uses

For temporary relief of local discomfort, itching, pain, soreness or burning in the perianal area associated with anorectal disorders.

Warnings

For external use only

When using this product

- do not exceed the recommeded daily dosage unless directed by a doctor
- do not put into the rectum by using fingers or any mechanical device or applicators

Stop the use and consult doctor if

- allergic reaction occurs
- rectal bleeding occurs
- redness, irritation, swelling, pain or other symptoms begin or increase
- condition worsens or does not improve within 7 days

KEEP OUT OF REACH OF CHILDREN

If swallowed, get medical help or contact a Poison Control Center right away

Directions

Adults and Children 12 years and older: When practical, cleanse the affected area with mild soap and warm water and rinse thoroughly. Gently dry by patting or blotting with toilet tissue or a soft cloth before application of this product. Apply to the affected area up to 6 times a day.

Children under 2 years: Consult a doctor

Other Information

- always keep the tube tightly closed
- Store at temperatures not exceeding 15°C-30°C (59°F-86°F)
- Protect from freezing

Inactive Ingredients

Benzyl Alcohol, Carbopol, Lecithin, Propylene Glycol, Tocopheryl Acetate, Water.

Questions or Comments

Contact our dedicated Customer Care at +1(877) 786 2001 or email us at support@shinpharma.com

Principal Display Panel

NDC 69903-004-10

Dr. Numb®

Lidocaine Cream

RAPID ABSORPTION!

Maximum Strength Pain Reliever

10g